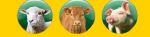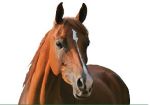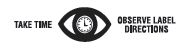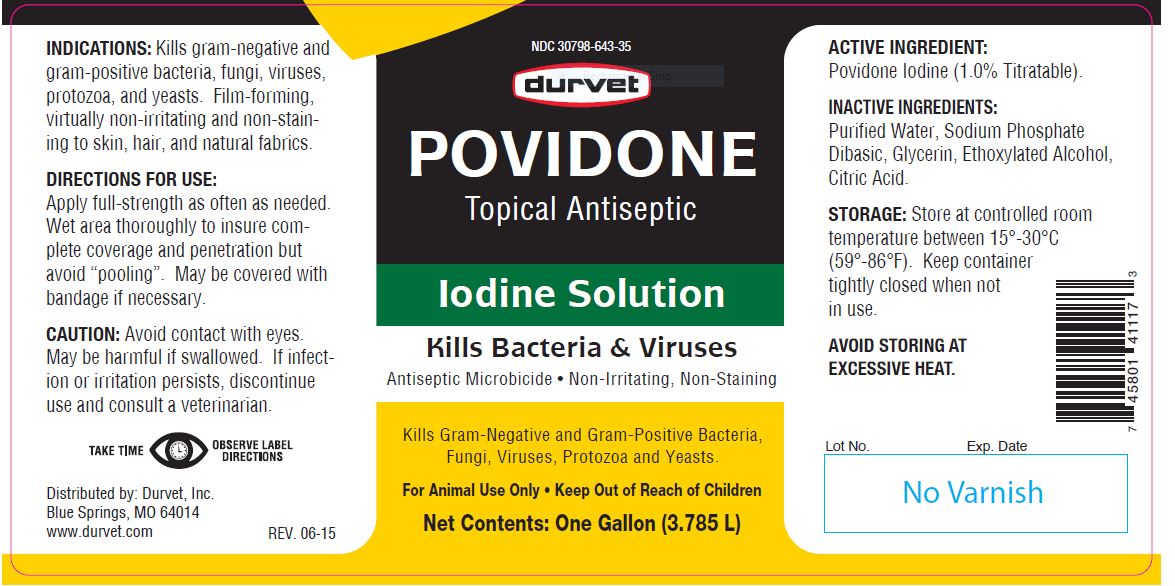 DRUG LABEL: POVIDONE Iodine
NDC: 30798-643 | Form: SOLUTION
Manufacturer: Durvet, Inc.
Category: animal | Type: OTC ANIMAL DRUG LABEL
Date: 20221116

ACTIVE INGREDIENTS: POVIDONE-IODINE 65.9 g/1 L

POVIDONE
Topical Antiseptic

PURPOSE

Kills Bacteria & Viruses

Iodine Solution

Antiseptic Microbicide
Non-Irritating, Non-Staining
Kills Gram-Negative and Gram-Positive Bacteria, Fungi, Viruses, Protozoa and Yeasts.

KEEP OUT OF REACH OF CHILDREN

For Animal Use Only • Keep Out of Reach of Children

INDICATIONS:

Kills gram-negative and gram-positive bacteria, fungi, viruses, protozoa, and yeasts. Film-forming, virtually non-irritating and non-staining to skin, hair, and natural fabrics.

DIRECTIONS FOR USE:

Apply full-strength as often as needed. Wet area thoroughly to insure complete coverage and penetration but avoid “pooling”. May be covered with bandage if necessary.

CAUTION:

Avoid contact with eyes. May be harmful if swallowed. If infection or irritation persists, discontinue use and consult a veterinarian.

ACTIVE INGREDIENT:

Povidone Iodine (1.0% Titratable).

INACTIVE INGREDIENTS:

Purified Water, Sodium Phosphate Dibasic, Glycerin, Ethoxylated Alcohol, Citric Acid.

STORAGE:

Store at controlled room temperature between 15°-30°C (59°-86°F). Keep container tightly closed when not in use.

AVOID STORING AT EXCESSIVE HEAT.

Net Contents:

32 fl oz (946 mL)

One Gallon (3.785 L)

INFORMATION FOR OWNERS/CAREGIVERS

Distributed by: Durvet, Inc.
Blue Springs, MO 64014
www.durvet.com